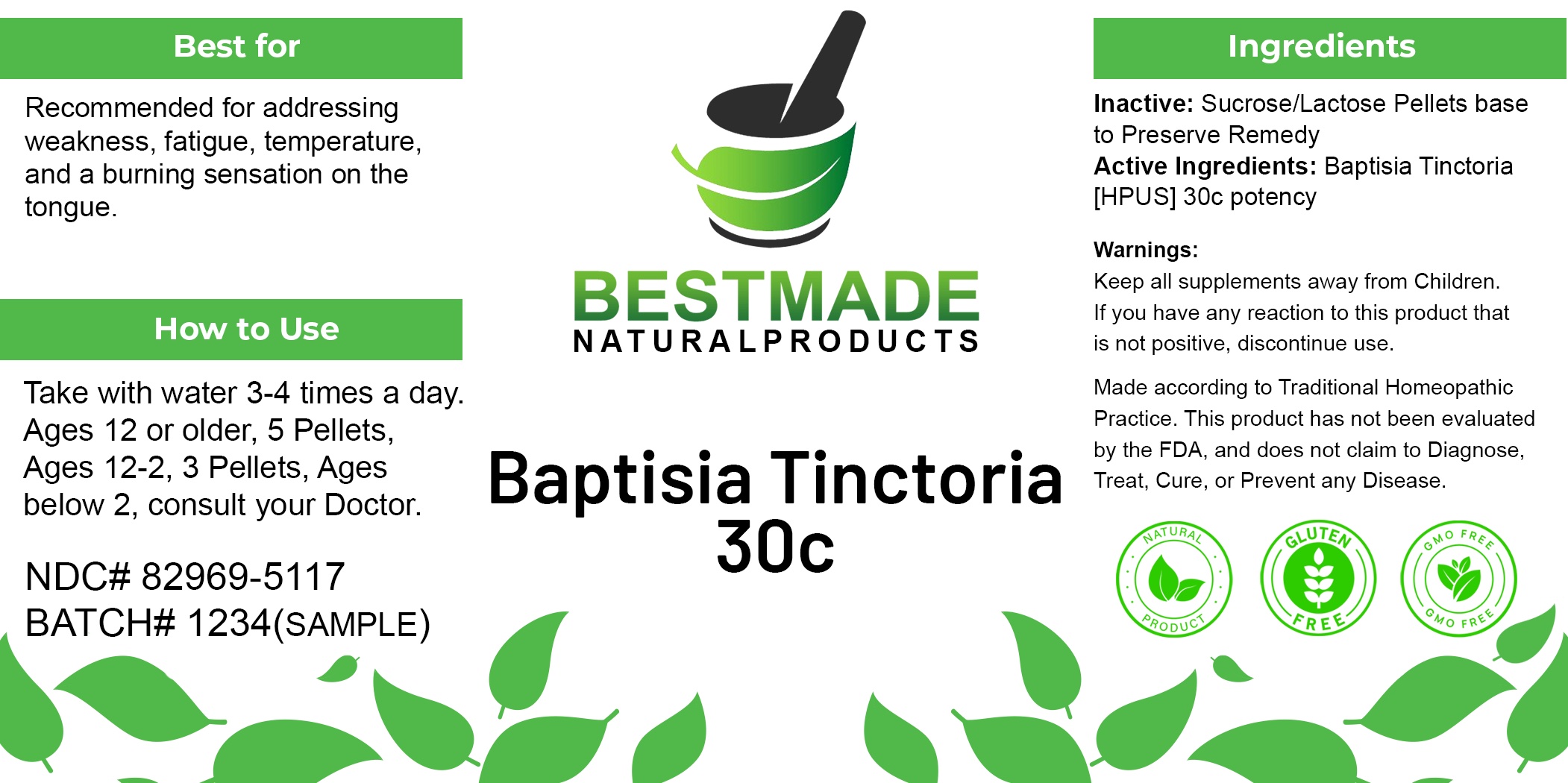 DRUG LABEL: Bestmade Natural Products Baptisia Tinctoria
NDC: 82969-5117 | Form: TABLET, SOLUBLE
Manufacturer: Bestmade Natural Products
Category: homeopathic | Type: HUMAN OTC DRUG LABEL
Date: 20241219

ACTIVE INGREDIENTS: BAPTISIA TINCTORIA 30 [hp_C]/30 [hp_C]
INACTIVE INGREDIENTS: LACTOSE 30 [hp_C]/30 [hp_C]; SUCROSE 30 [hp_C]/30 [hp_C]

BAPTISIA TINCTORIA 30C

DOSAGE AND ADMINISTRATION

How to Use:
Take with water 3-4 times a day.

Ages 12 or older: 5 Pellets
Ages 12-2: 3 Pellets
Ages below 2: Consult your doctor

INDICATIONS AND USAGE

Best for:
Recommended for addressing weakness, fatigue, temperature, and a burning sensation on the tongue.

INACTIVE INGREDIENT

Ingredients:

Inactive: Sucrose/Lactose Pellets base to Preserve Remedy

Warnings:

Keep all supplements away from children.
If you have any reaction to this product that is not positive, discontinue use.

Made according to Traditional Homeopathic Practice.
This product has not been evaluated by the FDA, and does not claim to diagnose, treat, cure, or prevent any disease.

ACTIVE INGREDIENT

Ingredients:

Active Ingredients: Baptisia Tinctoria [HPUS] 30c potency

Warnings:

Keep all supplements away from children.

PURPOSE

Best for:
Recommended for addressing weakness, fatigue, temperature, and a burning sensation on the tongue.

Entire Package label.